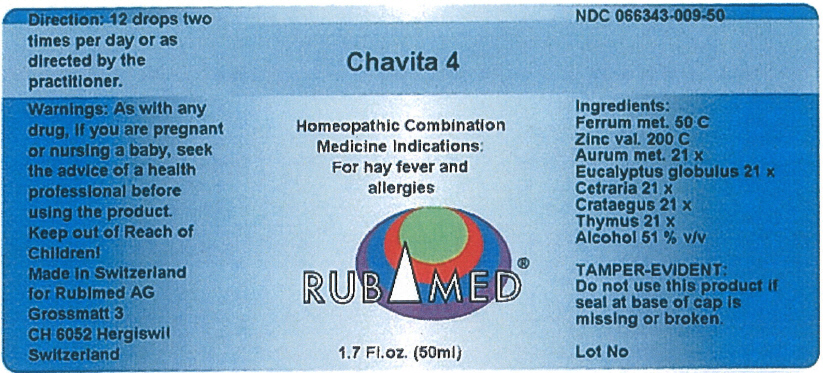 DRUG LABEL: Chavita 4
NDC: 66343-009 | Form: LIQUID
Manufacturer: RUBIMED AG
Category: otc | Type: HUMAN OTC DRUG LABEL
Date: 20150706

ACTIVE INGREDIENTS: IRON 50 [hp_C]/1 mL; ZINC VALERATE DIHYDRATE 200 [hp_C]/1 mL; GOLD 21 [hp_X]/1 mL; EUCALYPTUS GLOBULUS LEAF 21 [hp_X]/1 mL; CETRARIA ISLANDICA SUBSP. ISLANDICA 21 [hp_X]/1 mL; CRATAEGUS LAEVIGATA WHOLE 21 [hp_X]/1 mL; BOS TAURUS THYMUS 21 [hp_X]/1 mL
INACTIVE INGREDIENTS: ALCOHOL 0.51 mL/1 mL

Chavita 4

INDICATIONS AND USAGE

PURPOSE

Homeopathic Combination Medicine Indications: For hay fever and allergies

Ingredients

INACTIVE INGREDIENT

Ferrum met. 50 C
Zinc val. 200 C
Aurum met. 21 x
Eucalyptus globulus 21 x
Cetraria 21 x
Cratacgus 21 x
Thymus 21 x
Alcohol 51 % v/v

TAMPER-EVIDENT

Do not use this product if seal at base of cap is missing or broken.

Direction

12 drops two times per day or as directed by the practitioner.

Warnings

PREGNANCY OR BREAST FEEDING

As with any drug, if you are pregnant or nursing a baby, seek the advice of a health professional before using the product.

Keep out of Reach of Children!

PRINCIPAL DISPLAY PANEL - 50 mL Bottle Label

Chavita 4

Homeopathic Combination
Medicine Indications:
For hay fever and
allergies

RUBIMED®

1.7 Fl.oz. (50ml)